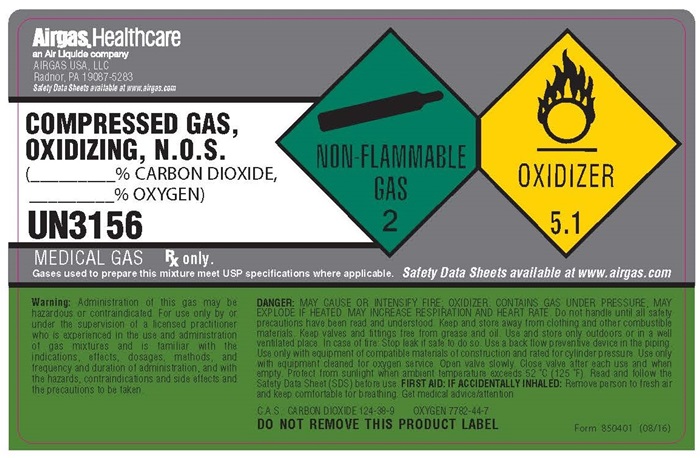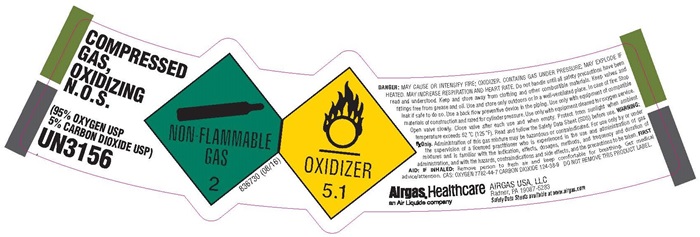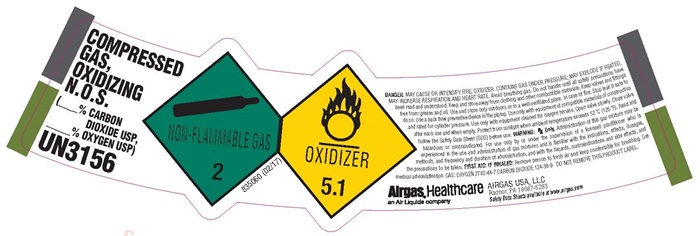 DRUG LABEL: Carbon Dioxide Oxygen Mix
NDC: 11054-114 | Form: GAS
Manufacturer: Airgas Usa, LLC
Category: prescription | Type: HUMAN PRESCRIPTION DRUG LABEL
Date: 20241001

ACTIVE INGREDIENTS: oxygen 950 mL/1 L
INACTIVE INGREDIENTS: CARBON DIOXIDE 50 mL/1 L

Carbon Dioxide Oxygen Mix 114

Airgas Carbon Dioxide -Oxygen Mix

Carbon Dioxide Oxygen

COMPRESSED GAS, OXIDIZING N.O.S (95% OXYGEN USP 5% CARBON DIOXIDE USP) UN3156

NON-FLAMMABLE GAS 2 OXIDIZER 5.1

836730 (06/16)

DANGER: MAY CAUSE OR INTENSIFY FIRE; OXIDIZER, CONTAINS GAS UNDER PRESSURE; MAY EXPLODE IF HEATED. MAY INCREASE RESPIRATION AND HEART RATE. Do not handle until all safety precautions have been read and understood. Keep and store away from clothing and other combustible materials. Keep valves and fittings from grease and oil. Use and store only outdoors or in a well-ventilated place. In case of fire: Stop leak if safe to do so. Use a back flow preventative device in the piping. Use only with equipment of compatible materials of construction and rated for cylinder pressure. Use only with equipment cleaned for oxygen service. Open valve slowly. Close valve after each use and when empty. Protect from sunlight when ambient temperature exceeds 52°C (125°F). Read and follow the Safety Data Sheet (SDS) before use. WARNING: Rx Only. Administration of this gas mixture may be hazardous or contraindicated. For use only by or under the supervision of a licensed practioner who is experienced in the use and administration of gas mixtures and is familiar with the indication, effects, dosages, methods, and frequency and duration of administration, and with the hazards, contraindications and side effects and the precautions to be taken. FIRST AID: IF INHALED: Remove person to fresh air and keep comfortable for breathing. Get medical advice/attention. CAS: OXYGEN 7782-44-7 CARBON DIOXIDE 124-38-9 DO NOT REMOVE THIS PRODUCT LABEL.

Airgas, Healthcare

An Air Liquide company

AIRGAS USA, LLC

Radnor, PA 19087-5283

Safety Data Sheet available at www.airgas.com

Airgas Carbon Dioxide -Oxygen Mix Shoulder Label

Carbon Dioxide Oxygen

COMPRESSED GAS, OXIDIZING N.O.S.

(____% CARBON DIOXIDE USP, ____% OXYGEN USP)

UN3156

NON-FLAMMABLE GAS 2

OXIDIZER 5.1

835060 (02/17)

DANGER: MAY CAUSE OR INTENSIFY FIRE; OXIDIZER, CONTAINS GAS UNDER PRESSURE; MAY EXPLODE IF HEATED. MAY INCREASE RESPIRATION AND HEART RATE. Do not handle until all safety precautions have been read and understood. Keep and store away from clothing and other combustible materials. Keep valves and fittings from grease and oil. Use and store only outdoors or in a well-ventilated place. In case of fire: Stop leak if safe to do so. Use a back-flow preventative device in the piping. Use only with equipment of compatible materials of construction and rated for cylinder pressure. Use only with equipment cleaned for oxygen service. Open valve slowly. Close valve after each use and when empty. Protect from sunlight when ambient temperature exceeds 52°C (125°F). Read and follow the Safety Data Sheet (SDS) before use. WARNING: Rx Only. Administration of this gas mixture may be hazardous or contraindicated. For use only by or under the supervision of a licensed practioner who is experienced in the use and administration of gas mixtures and is familiar with the indication, effects, dosages, methods, and frequency and duration of administration, and with the hazards, contraindications and side effects and the precautions to be taken. FIRST AID: IF INHALED: Remove person to fresh air and keep comfortable for breathing. Get medical advice/attention. CAS: OXYGEN 7782-44-7 CARBON DIOXIDE 124-38-9 DO NOT REMOVE THIS PRODUCT LABEL.

Airgas, Healthcare

An Air Liquide company

AIRGAS USA, LLC

Radnor, PA 19087-5283

Safety Data Sheet available at www.airgas.com

Airgas Carbon Dioxide -Oxygen Mix Body Label

Carbon Dioxide Oxygen

Airgas, Healthcare an Air Liquide Company

AIRGAS USA, LLC

Radnor, PA 19087-5283

Safety Data Sheets Available at www.airgas.com

COMPRESSED GAS, OXIDIZING, N.O.S.

(____% CARBON DIOXIDE USP, ____% OXYGEN USP)

UN3156

NON-FLAMMABLE GAS 2

OXIDIZER 5.1

MEDICAL GAS Rx only.

Gases used to prepare this mixture meet USP specifications where applicable. Safety Data Sheets available at www.airgas .com

Warning: Administration of this gas may be hazardous or contraindicate for use only by or under the supervision of a licensed practitioner who is experienced in the use and administration of gas mixtures and is familiar with the indications, affects, dosages, methods, and frequency and duration of administration and with the hazards, contraindications and side effects and precautions to be taken. DANGER: MAY CAUSE OR INTINSIFY FIRE, OXIDIZER, CONTAINS GAS UNDER PRESSURE. MAY EXPLODE IF HEATED MAY INCREASE RESPIRATION AND HEART RATE. Do not handle until all safety precautions have been read and understood. Keep and store away for clothing and other combustible materials. Keep valves and fitting free from grease and oil. Use and store only outdoors or in a well-ventilated place. In case of fire: Stop leak if safe to do so. Use a back-flow preventative device in the piping. Use only with equipment of compatible materials of construction and rated for cylinder pressure. Use only with equipment cleaned for oxygen service. Open valve slowly. Close valve after each use and when empty. Protect for sunlight when ambient temperature exceeds 52°C (125°F). Read and follow the Safety Data Sheet (SDS) before use. FIRST AID: IF ACCIDENTALLY INHALED: Remove person to fresh air and keep comfortable for breathing. Get medical advice/attention.

C.A.S. CARBON DIOXIDE 124-38-9 OXYGEN 7782-44-7

DO NOT REMOVE THIS PRODUCT LABEL

Form 850401 (08/16)